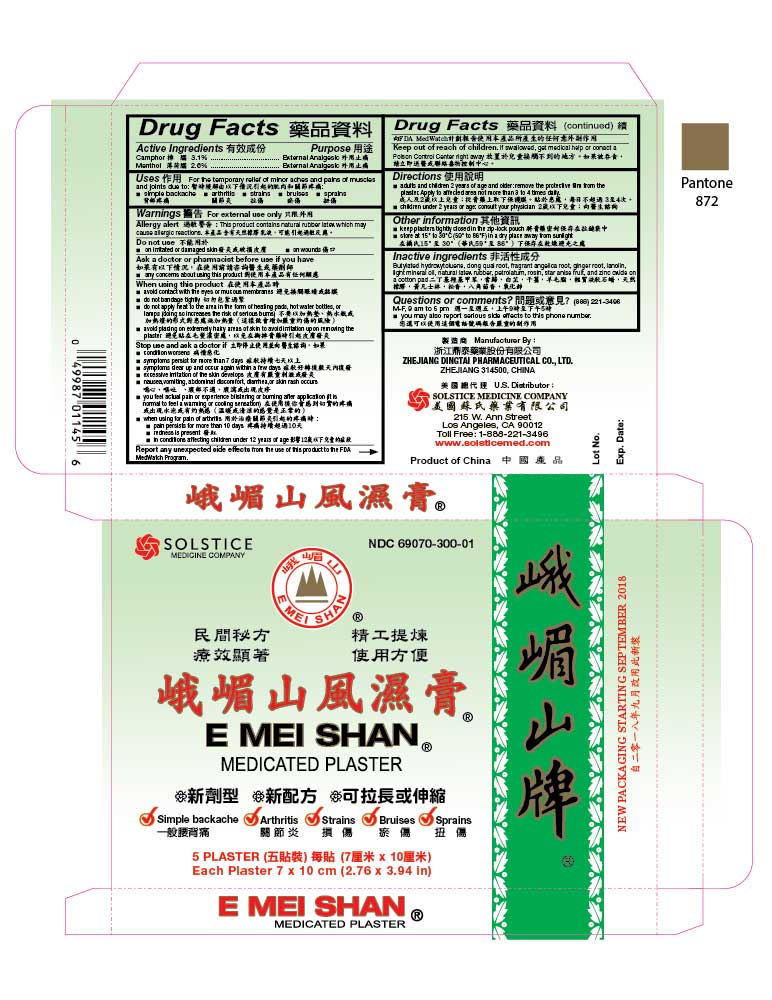 DRUG LABEL: E MEI SHAN MEDICATED
NDC: 69070-300 | Form: PLASTER
Manufacturer: Zhejiang Dingtai Pharmaceutical Co., Ltd
Category: otc | Type: HUMAN OTC DRUG LABEL
Date: 20251110

ACTIVE INGREDIENTS: CAMPHOR (SYNTHETIC) 31 mg/1 1; MENTHOL 26 mg/1 1
INACTIVE INGREDIENTS: BUTYLATED HYDROXYTOLUENE; ANGELICA SINENSIS ROOT; ANGELICA DAHURICA ROOT; GINGER; LANOLIN; LIGHT MINERAL OIL; NATURAL LATEX RUBBER; PETROLATUM; ROSIN; STAR ANISE; ZINC OXIDE

DRUG FACTS

Active Ingredients
Camphor 3.1%
Menthol 2.6%

Purpose
External Analgesic
External Analgesic

Uses
For the temporary relief of minor aches and pains of muscles and joints due to:
■ simple backache ■ arthritis ■ strains ■ bruises ■ sprains

Warnings
For external use only

Allergy alert: This product contains natural rubber latex which may cause allergic reactions

Report any unexpected side effects from the use of this product to the FDA MedWatch Program

Do not use
■ on irritated or damaged skin ■ on wounds

Ask a doctor or pharmacist before use if you have
■ any concerns about using this product

When using this product
■ avoid contact with the eyes or mucous membranes
■ do not bandage tightly
■ do not apply heat to the area in the form of heating pads, hot water bottles, or lamps (doing so increases the risk of serious burns)
■ avoid placing on extremely hairy areas of skin to avoid irritation upon removing the plaster

Stop use and ask a doctor if
■ condition worsens
■ symptoms persist for more than 7 days
■ symptoms clear up and occur again within a few days
■ excessive irritation of the skin develops
■ nausea, vomiting, abdominal discomfort, diarrhea, or skin rash occurs
■ you feel actual pain or experience blistering or burning after application (it is normal to feel a warming or cooling sensation)
■ when using for pain of arthritis:
■ pain persists for more than 10 days ■ redness is present
■ in conditions affecting children under 12 years of age

Keep out of reach of children. If swallowed, get medical help or contact a Poison Control Center right away.

Directions
■ adults and children 2 years of age and older: remove the protective film from the plaster. Apply to affected area not more than 3 to 4 times daily.
■ children under 2 years of age: consult your physician

Other information
■ keep plasters tightly closed in the zip-lock pouch
■ store at 15º to 30º C (59º to 86º F) in a dry place away from sunlight

Inactive ingredients
Butylated hydroxytoluene, dong quai root, fragrant angelica root, ginger root, lanolin, light mineral oil, natural latex rubber, petrolatum, rosin, star anise fruit, and zinc oxide on a cotton pad

Questions or comments?
(888) 221-3496 M-F 9 am to 5 pm
■ you may also report serious side effects to this phone number

PACKAGE LABEL

E MEI SHAN MEDICATED PLASTER

NDC 69070-300-01

Simple backache, Arthritis, Strains, Bruises, Sprains

5 Plaster
Each Plaster 7 x 10 cm (2.76 x 3.94 in)